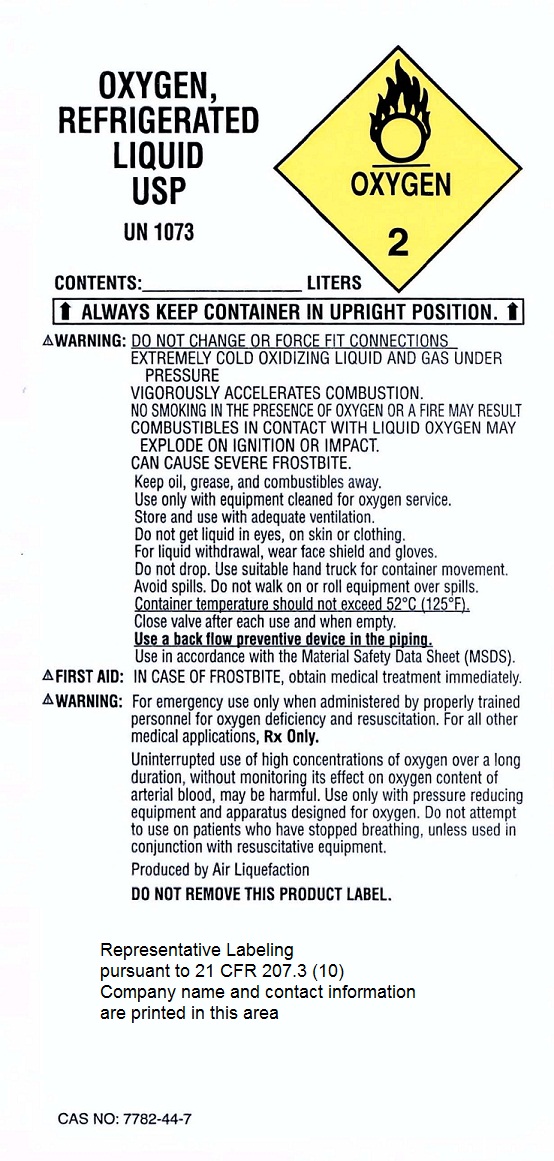 DRUG LABEL: Oxygen
NDC: 44356-0001 | Form: GAS
Manufacturer: Linco Medical & Supply Inc
Category: prescription | Type: HUMAN PRESCRIPTION DRUG LABEL
Date: 20110218

ACTIVE INGREDIENTS: Oxygen 99 L/100 L

Oxygen

Principal for Oxygen Product

Liquid Label